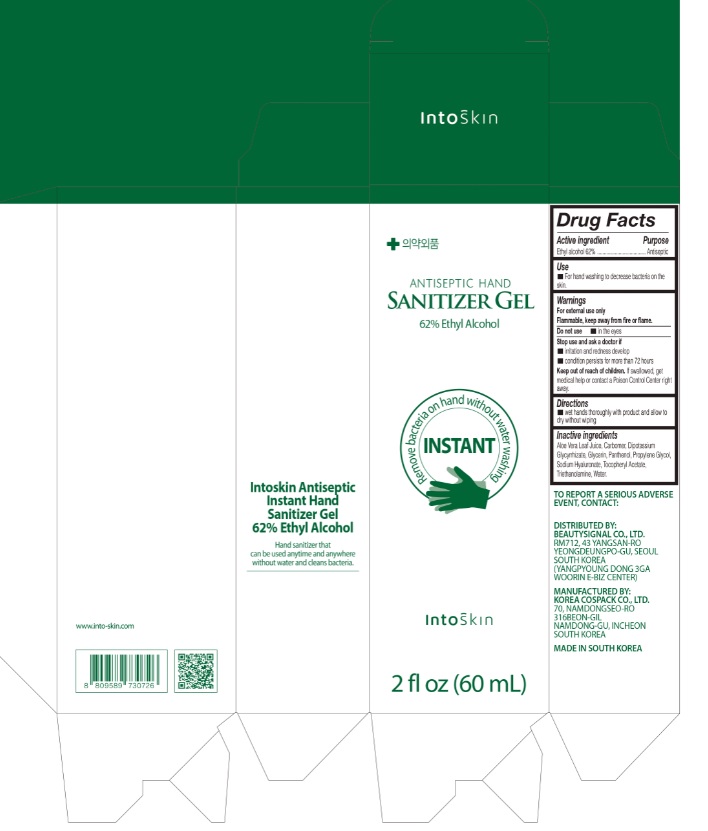 DRUG LABEL: INTOSKIN ANTISEPTIC HAND SANITIZER Gel
NDC: 76654-662 | Form: GEL
Manufacturer: Beauty Signal Co., Ltd.
Category: otc | Type: HUMAN OTC DRUG LABEL
Date: 20200424

ACTIVE INGREDIENTS: ALCOHOL 37.2 mL/60 mL
INACTIVE INGREDIENTS: GLYCERIN; CARBOMER HOMOPOLYMER, UNSPECIFIED TYPE; WATER; PROPYLENE GLYCOL; PANTHENOL; GLYCYRRHIZINATE DIPOTASSIUM; ALOE VERA LEAF; .ALPHA.-TOCOPHEROL ACETATE; HYALURONATE SODIUM; TROLAMINE

INTOSKIN ANTISEPTIC HAND SANITIZER GEL 60 ML (TUBE+BOX) : 76654-662-02